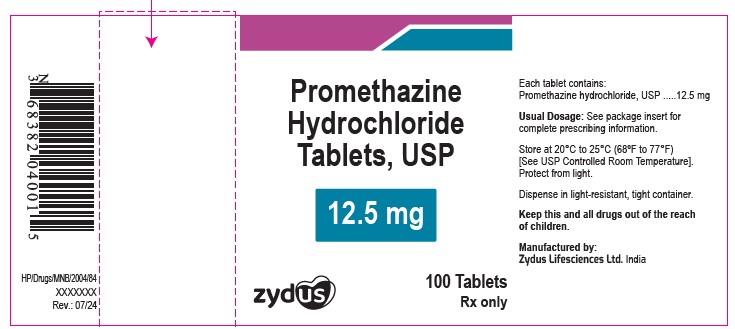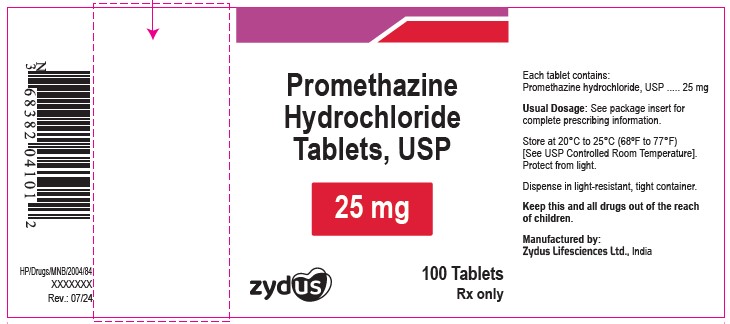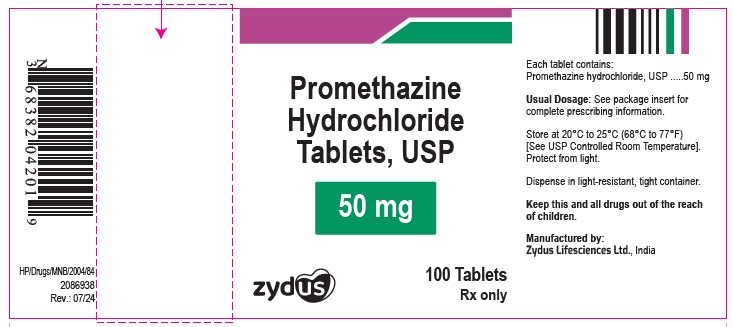 DRUG LABEL: Promethazine Hydrochloride
NDC: 65841-040 | Form: TABLET
Manufacturer: Zydus Lifesciences Limited
Category: prescription | Type: HUMAN PRESCRIPTION DRUG LABEL
Date: 20241204

ACTIVE INGREDIENTS: PROMETHAZINE HYDROCHLORIDE 12.5 mg/1 1
INACTIVE INGREDIENTS: LACTOSE MONOHYDRATE; MAGNESIUM STEARATE; HYDROXYPROPYL CELLULOSE, UNSPECIFIED; HYDROXYPROPYL CELLULOSE, LOW SUBSTITUTED

Promethazine Hydrochloride Tablets USP

PACKAGE LABEL.PRINCIPAL DISPLAY PANEL

NDC 65841-040-01 in bottle of 100 tablets

Promethazine Hydrochloride Tablets USP, 12.5 mg

Rx only

100 tablets

NDC 65841-041-01 in bottle of 100 tablets

Promethazine Hydrochloride Tablets USP, 25 mg

Rx only

100 tablets

NDC 65841-042-01 in bottle of 100 tablets

Promethazine Hydrochloride Tablets USP, 50 mg

Rx only

100 tablets